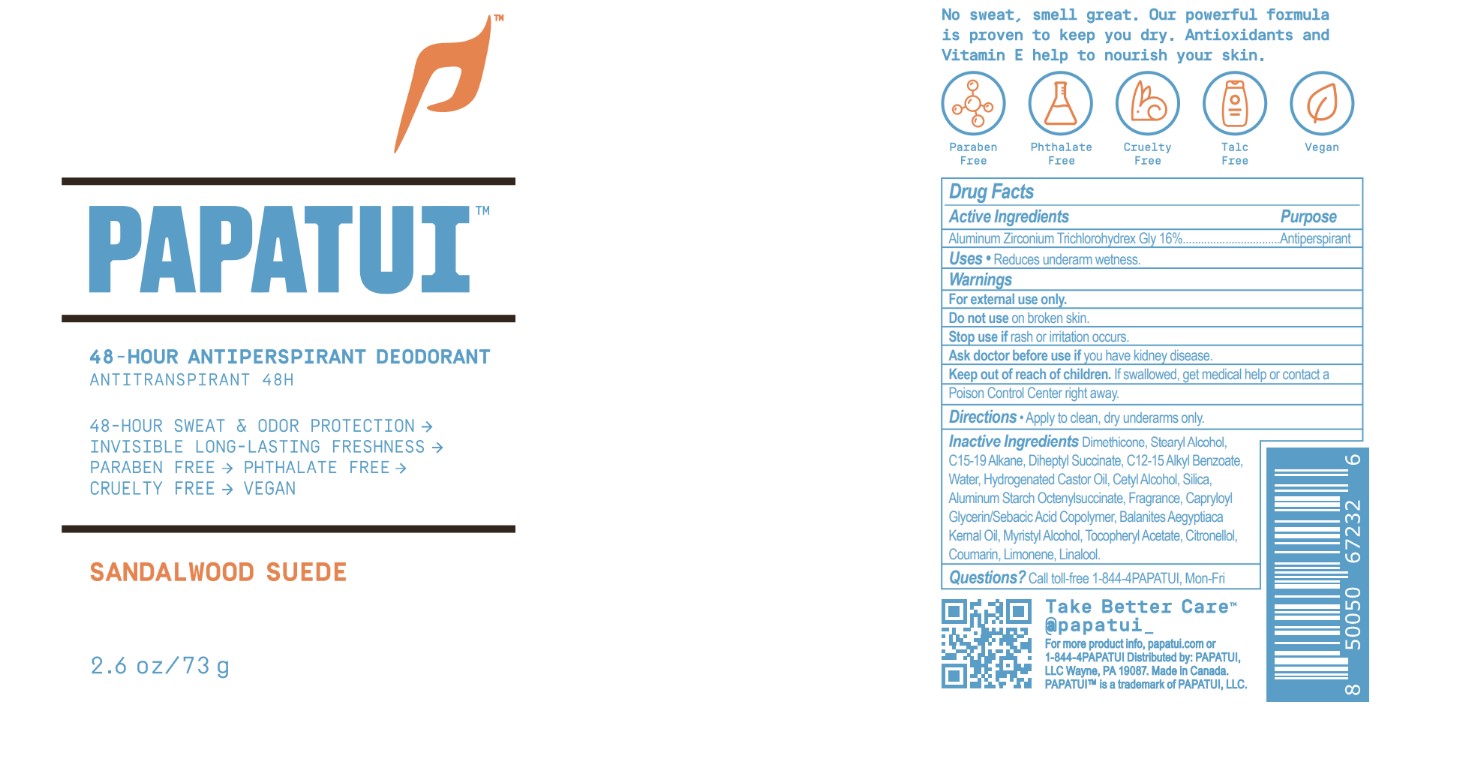 DRUG LABEL: Papatui Antiperspirant Deodorant Sandalwood Suede
NDC: 83850-103 | Form: STICK
Manufacturer: PAPATUI LLC
Category: otc | Type: HUMAN OTC DRUG LABEL
Date: 20241211

ACTIVE INGREDIENTS: ALUMINUM ZIRCONIUM TRICHLOROHYDREX GLY 16 g/100 g
INACTIVE INGREDIENTS: STEARYL ALCOHOL; ALUMINUM STARCH OCTENYLSUCCINATE; SILICON DIOXIDE; COUMARIN; LIMONENE, (+)-; .BETA.-CITRONELLOL, (R)-; LINALOOL, (+)-; .ALPHA.-TOCOPHEROL ACETATE; C15-19 ALKANE; ALKYL (C12-15) BENZOATE; HYDROGENATED CASTOR OIL; CETYL ALCOHOL; CAPRYLOYL GLYCERIN/SEBACIC ACID COPOLYMER (2000 MPA.S); BALANITES AEGYPTIACA SEED OIL; MYRISTYL ALCOHOL; DIMETHICONE; WATER

Papatui Antiperspirant Deodorant Sandalwood Suede (NDC 83850-103)

DESCRIPTION

PAPATUI™

48-HOUR ANTIPERSPIRANT DEODORANT

ANTITRANSPIRANT 48H

48-HOUR SWEAT & ODOR PROTECTION ->

INVISIBLE LONG-LASTING FRESHNESS ->

PARABEN FREE -> PHTHALATE FREE ->

CRUELTY FREE -> VEGAN

Sandalwood Suede

2.6 oz/ 73 g

Drug Facts

Active Ingredients

Aluminum Zirconium Trichlorohydrex Gly 16%

Purpose

Antiperspirant

Uses

Reduces underarm wetness.

Warnings

For external use only.
Do not use on broken skin.
Stop use if rash or irritation occurs.
Ask doctor before use if you have kidney disease.

DOSAGE AND ADMINISTRATION

For external use only.

Keep out of reach of children. If swallowed, get medical help or contact a Poison Control Center right away

Directions

Apply to clean, dry underarms only.

Inactive Ingredients

Dimethicone, Stearyl Alcohol, C15-19 Alkane, Diheptyl Succinate, C12-15 Alkyl Benzoate,
Water, Hydrogenated Castor Oil, Cetyl Alcohol, Silica, Aluminum Starch Octenylsuccinate, Fragrance, Capryloyl
Glycerin/Sebacic Acid Copolymer, Balanites Aegyptiaca Kernal Oil, Myristyl Alcohol, Tocopheryl Acetate, Citronellol, Coumarin, Limonene, Linalool.

QUESTIONS

Questions? Call toll-free 1-844-4PAPATUI, Mon-Fr